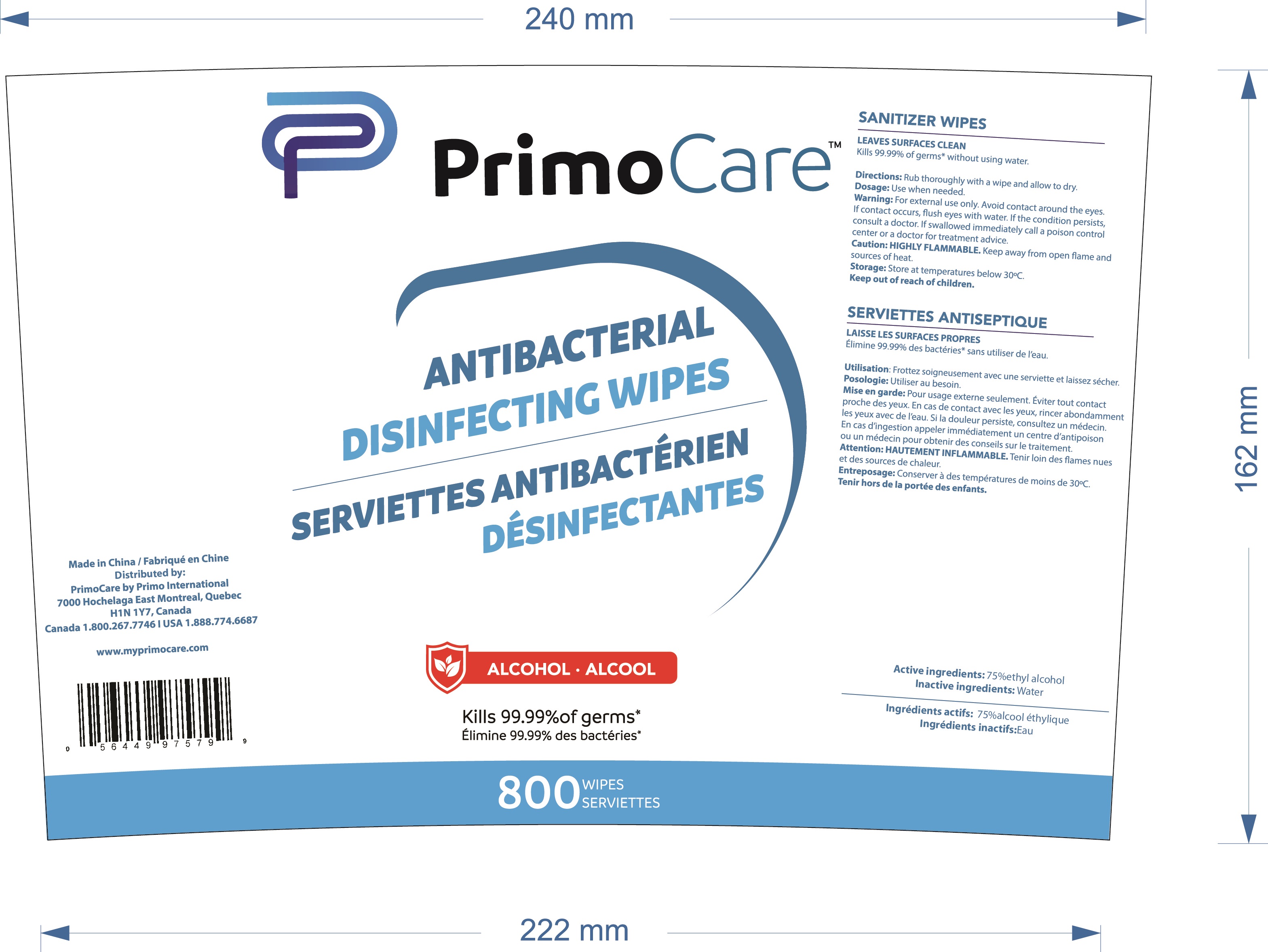 DRUG LABEL: Alcohol wipes (75% Alcohol)
NDC: 79795-003 | Form: CLOTH
Manufacturer: NanTong Guarder Medical Technology Co.,Ltd.
Category: otc | Type: HUMAN OTC DRUG LABEL
Date: 20201109

ACTIVE INGREDIENTS: ALCOHOL 0.75 g/1 1
INACTIVE INGREDIENTS: WATER

Alcohol wipes (75% Alcohol)

Active Ingredient(s)

Alcohol 75% v/v. Purpose: Antiseptic

Purpose

Antiseptic

Use

Alcohol wet wipe to help reduce bacteria that potentially can cause disease. For use when soap and water are not available.

Warnings

For external use only. Flammable. Keep away from heat or flame

Do not use

- in children less than 2 months of age
- on open skin wounds

When using this product keep out of eyes, ears, and mouth. In case of contact with eyes, rinse eyes thoroughly with water.
Stop use and ask a doctor if irritation or rash occurs. These may be signs of a serious condition.
Keep out of reach of children. If swallowed, get medical help or contact a Poison Control Center right away.

Stop use and ask a doctor if irritation or rash occurs. These may be signs of a serious condition.

Keep out of reach of children. If swallowed, get medical help or contact a Poison Control Center right away.

Directions

Wet hands thoroughly with product and allow to dry.

Dicard wipes in trash receptacle after use. Do not flush.

Children under 6 years of age should be supervised when using this product.

Other information

- Store between 15-30C (59-86F)
- Avoid freezing and excessive heat above 40C (104F)

Inactive ingredients

Aqua

Package Label - Principal Display Panel

800wipes in onebox NDC: 79795-003-09